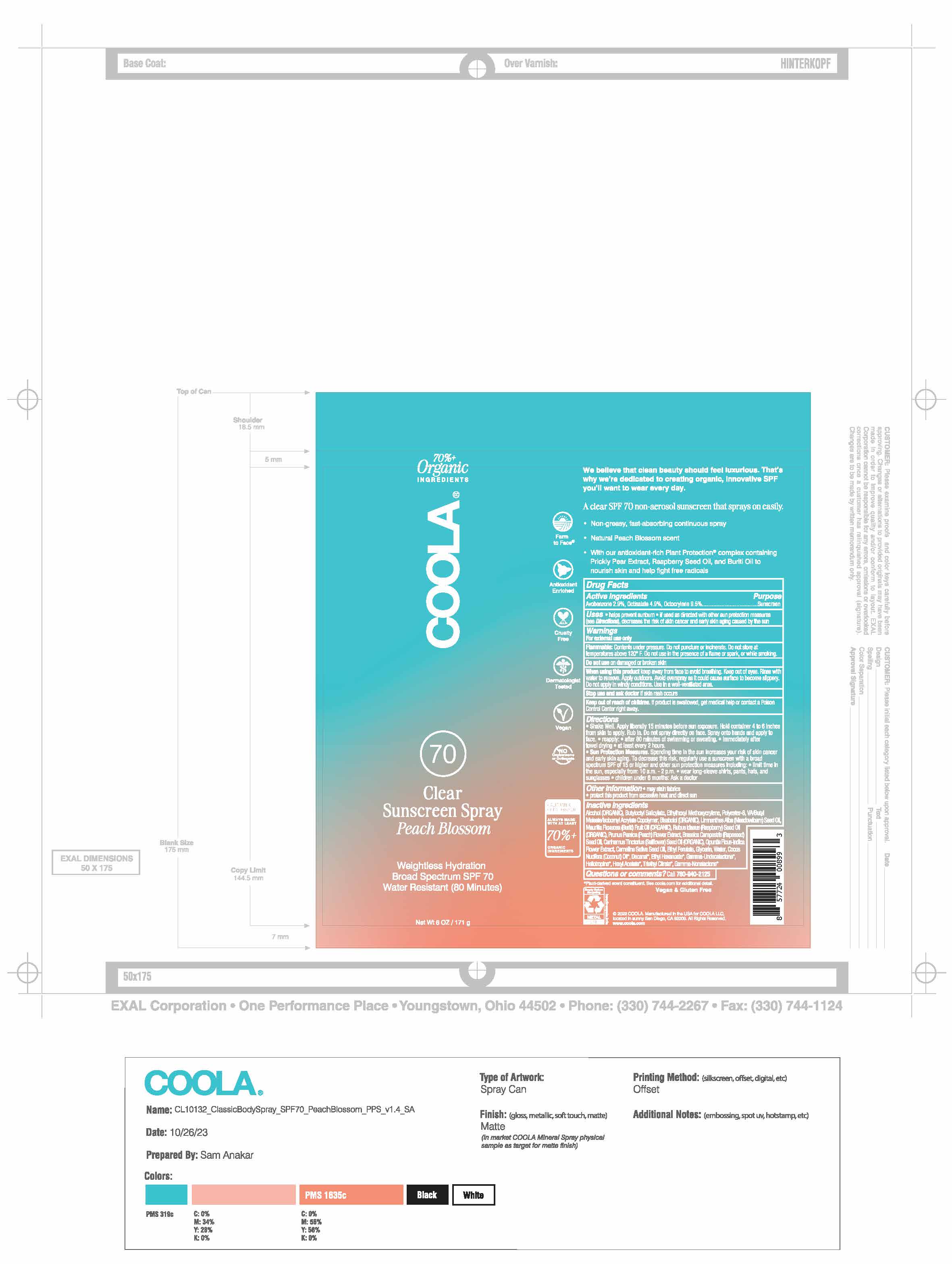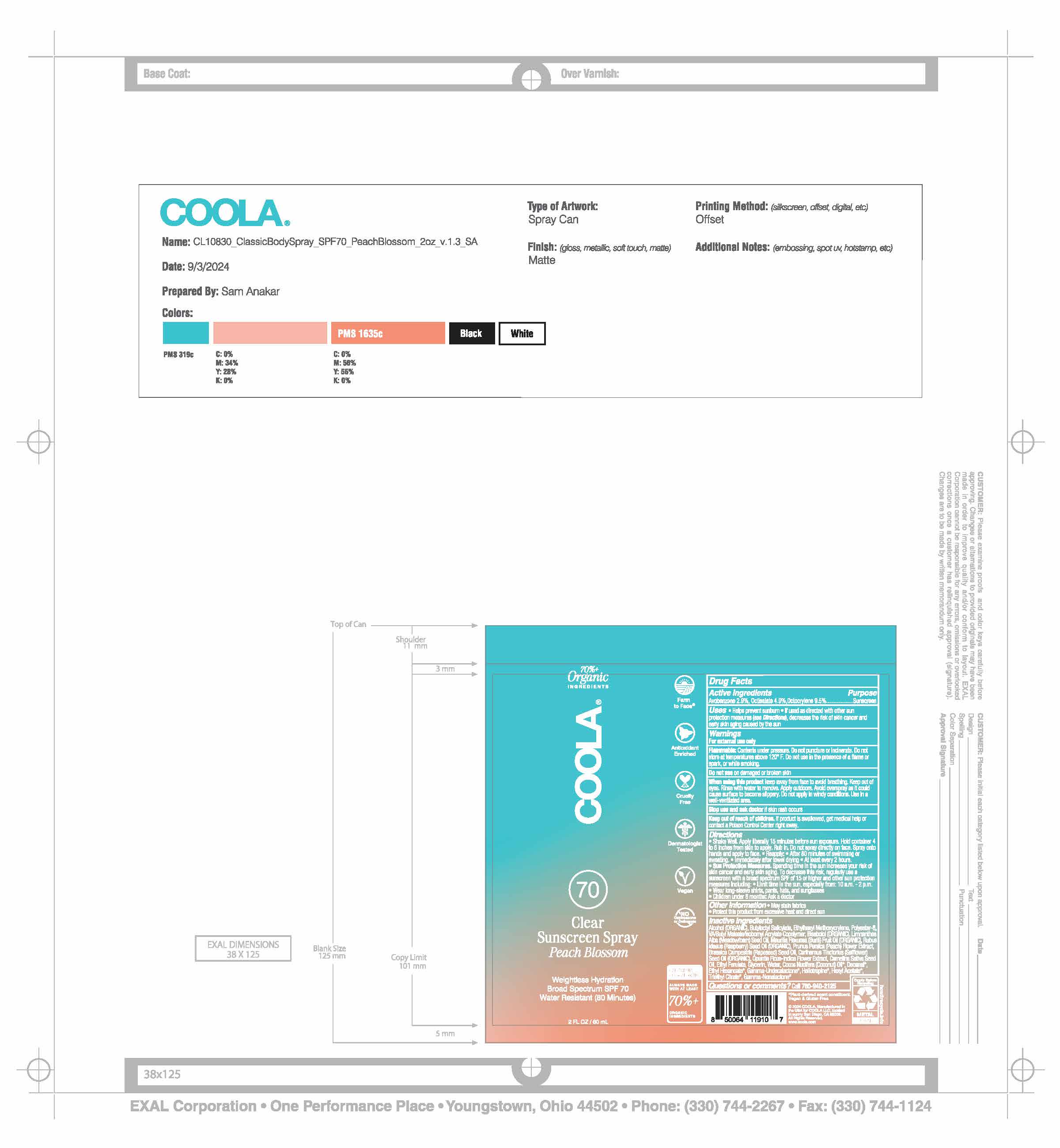 DRUG LABEL: COOLA Classic Body SPF 70 Peach Blossom
NDC: 79753-058 | Form: SPRAY
Manufacturer: COOLA, LLC
Category: otc | Type: HUMAN OTC DRUG LABEL
Date: 20250225

ACTIVE INGREDIENTS: AVOBENZONE 2.9 g/100 mL; OCTISALATE 4.9 g/100 mL; OCTOCRYLENE 9.5 g/100 mL
INACTIVE INGREDIENTS: GLYCERIN; ETHYLHEXYL METHOXYCRYLENE; DIBUTYL MALEATE; ETHYL CAPROATE; HEXYL ACETATE; TRIETHYL CITRATE; DECANAL; COCONUT OIL; WATER; PIPERONAL; POLYESTER-8 (1400 MW, CYANODIPHENYLPROPENOYL CAPPED); LEVOMENOL; .GAMMA.-UNDECALACTONE; .GAMMA.-NONALACTONE; OPUNTIA FICUS-INDICA FLOWER; VINYL ACETATE; ISOBORNYL ACRYLATE; ETHYL FERULATE; BRASSICA RAPA SUBSP. OLEIFERA OIL; CAMELINA SATIVA SEED OIL; ALCOHOL; SAFFLOWER OIL; MEADOWFOAM SEED OIL; MAURITIA FLEXUOSA FRUIT OIL; RASPBERRY SEED OIL; PRUNUS PERSICA FLOWER; BUTYLOCTYL SALICYLATE

Coola Classic Body Spray SPF 70 - Peach Blossom

ACTIVE INGREDIENT

Avobenzone - 2.9%

Octisalate - 4.9%

Octocrylene - 9.5%

PURPOSE

Sunscreen

Uses

- Helps prevent sunburn
- If used as directed with other sun protection measures (see Directions), decreases the nsk of skin cancer and early skin aging caused by the sun

WARNINGS

- For external use only
- Flammable: Contents under pressure. Do not puncture or incinerat. Do not store at temperatures above 120 F. Do not use in the presence of a flame or spark, or while smoking.
- Do not use on damaged or broken skin.
- When using this product keep away from face to avoid breathing. Keep out of eyes. Rinse with water to remove. Apply outdoors. Avoid overspray as it could cause surface to become slippery. Do not apply in windy conditions. Use in a well-ventilated area.
- Stop use and ask a doctor if rash occurs.

Keep out of reach of children. If product is swallowed, get medical help or contact a Poison Control Center right away.

Directions

- Shake Well
- Apply liberally 15 minutes before sun exposure.
- Hold container 4 to 6 inches from skin to apply.
- Rub in. Do not spray directly on face.
- Spray onto hands and apply to face.
- Reapply: After 80 minutes of swimming or sweating. Immediately after towel drying. At least every 2 hours.
- Sun Protection Measures. Spending time in the sun increases your risk of skin cancer and early skin aging. To decrease this risk, regularly use a sunscreen with a Broad Spectrum SPF value of 15 or higher and other sun protection measures including: • Limit time in the sun especially from 10 a.m. – 2 p.m. • Wear long-sleeved shirts, pants, hats, and sunglasses.
- Children under six months: Ask a doctor.

INACTIVE INGREDIENT

Alcohol (ORGANIC), Butyloctyl Salicylate, Ethylhexyl Methoxycrylene, Polyester-8, VA/Butyl Maleate/Isobornyl Acrylate Copolymer, Bisabolol (ORGANIC), Limnanthes Alba (Meadowfoam) Seed Oil, Mauritia Flexuosa (Buriti) Fruit Oil (ORGANIC), Rubus Idaeus (Raspberry) Seed Oil (ORGANIC), Prunus Persica (Peach) Flower Extract, Brassica Campestris (Rapeseed) Seed Oil, Carthamus Tinctorius (Safflower) Seed Oil (ORGANIC), Opuntia Ficus-Indica Flower Extract, Camelina Sativa Seed Oil, Ethyl Ferulate, Glycerin, Water, Coconus Nucifera (Coconut) Oil, Decanal, Ethyl Hexanoate, Gamma-Undecalactone, Heliotropine, Hexyl Acetate, Triethyl Citrate, Gamma-Nonalactone

OTHER SAFETY INFORMATION

- May stain fabrics
- Protect this product from excessive heat and direct sun

QUESTIONS

Call 760-940-2125